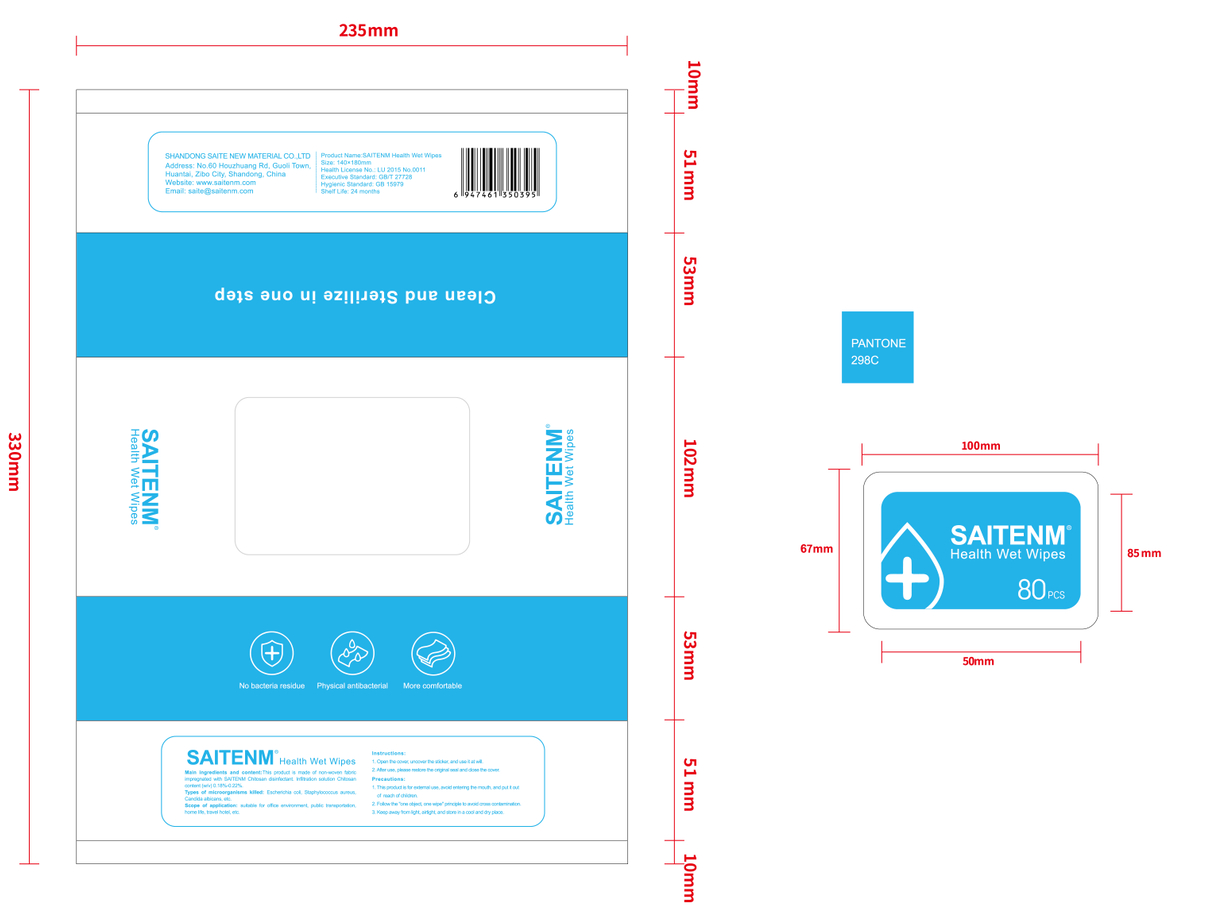 DRUG LABEL: SAITENM Health Wet wipes
NDC: 92389-001 | Form: CLOTH
Manufacturer: Shandong Saite New Material Co., Ltd.
Category: otc | Type: HUMAN OTC DRUG LABEL
Date: 20200811

ACTIVE INGREDIENTS: BENZALKONIUM 0.75 g/80 1; CHLORHEXIDINE GLUCONATE 0.75 g/80 1
INACTIVE INGREDIENTS: POLYSORBATE 20; LAURYLPYRIDINIUM CHLORIDE; PROPYLENE GLYCOL; GLYCERIN; CAPRYLIC ALCOHOL; WATER; PHENOXYETHANOL

DOSAGE AND ADMINISTRATION

Keep away from light, airtight, and store in a cool and dry place.

INACTIVE INGREDIENT

Glycerin, dodecyl pyridine chloride, Polysorbate-20, chitosan quaternary ammonium salt, water, chlorhexidine gluconate, propylene glycol, silylated polydimethylsiloxane, octanol, phenoxyethanol.

INDICATIONS AND USAGE

1. Open the cover, uncover the sticker, and use it at will.
2. After use, please restore the original seal and close the cover.

ACTIVE INGREDIENT

Benzalkonium,chlorhexidine gluconate

keep out of reach of children

PURPOSE

Disinfection
Sterilization
No Rinseing

WARNINGS

1. This product is for extemal use, avoid entering the mouth, and put it out of reach of children.
2. Follow the "one object, one wipe" principle to avoid cross contamination.
3. Keep away from light, airtight, and store in a cool and dry place.